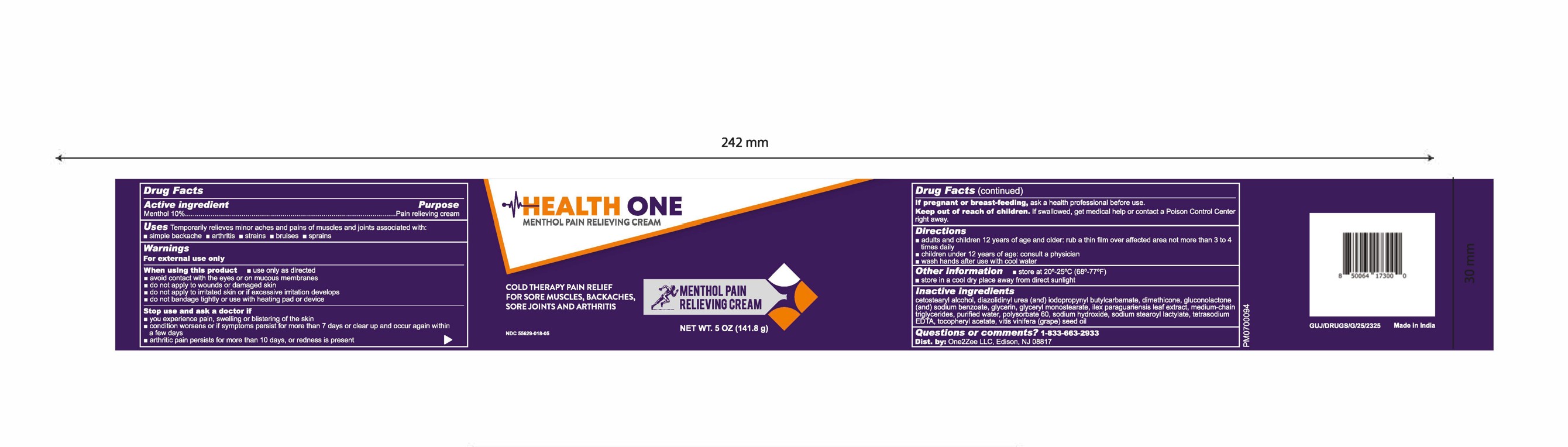 DRUG LABEL: Menthol Pain Relieving Cream with Menthol 10%
NDC: 55629-018 | Form: CREAM
Manufacturer: ONE2ZEE LIMITED LIABILITY COMPANY
Category: otc | Type: HUMAN OTC DRUG LABEL
Date: 20250505

ACTIVE INGREDIENTS: MENTHOL 0.1 g/1 g
INACTIVE INGREDIENTS: CETOSTEARYL ALCOHOL; DIAZOLIDINYL UREA; DIMETHICONE; GLUCONOLACTONE; SODIUM BENZOATE; GLYCERIN; GLYCERYL MONOSTEARATE; ILEX PARAGUARIENSIS LEAF; MEDIUM-CHAIN TRIGLYCERIDES; WATER; POLYSORBATE 60; SODIUM HYDROXIDE; SODIUM STEAROYL LACTYLATE; TETRASODIUM EDTA; .ALPHA.-TOCOPHEROL ACETATE; VITIS VINIFERA (GRAPE) SEED OIL

Menthol Pain Relieving Cream - Menthol 10%

Active Ingredient:

Menthol 10%

Purpose

- Pain relieving cream

Uses:

Temporarily relieves minor aches and pains of muscles and joints associated with:

- simple
- backache
- arthritis
- strains
- bruises
- sprains

Warnings:

- For external use only. If condition worsens or does not improve within 7 days, consult a doctor.

When using this product,

- use only as directed
- avoid contact with the eyes or on mucous membranes
- do not apply to wounds or damaged skin
- do not apply to irritated skin or if excessive irritation develops
- do not bandage tightly or use with heating pad or device

Directions:

- adults and children 12 years of age and older: rub a thin film over affected area not more than 3 to 4 times daily
- children under 12 years of age: consult a physician
- wash hands after use with cool water

Adults and children 12 years and older: For optimum results cleanse the affected area with mild soap and warm water and rinse thoroughly. Gently dry by patting or blotting with toilet tissue or a clean, soft cloth before application of this product. Apply externally up to 6 times per day.

Keep out of reach of children. If swallowed, get medical help or contact a Poison Control Center right away.

Inactive Ingredients

Caprylic/Capric Triglyceride, Cetearyl Alcohol, Diazolidinyl Urea, Dimethicone, Gluconolactone, Glycerin, Glyceryl Stearate, Ilex Paraguariensis Leaf Extract, Iodopropynyl Butylcarbamate, Polysorbate 60, Sodium Benzoate, Sodium Hydroxide, Sodium Stearoyl Lactylate, Tetrasodium EDTA, Tocopheryl Acetate, Vitis Vinifera (Grape) Seed Oil, Water

Other Information:

store at 20-25°C (68-77°F)  store in a cool dry place away from direct sunlight